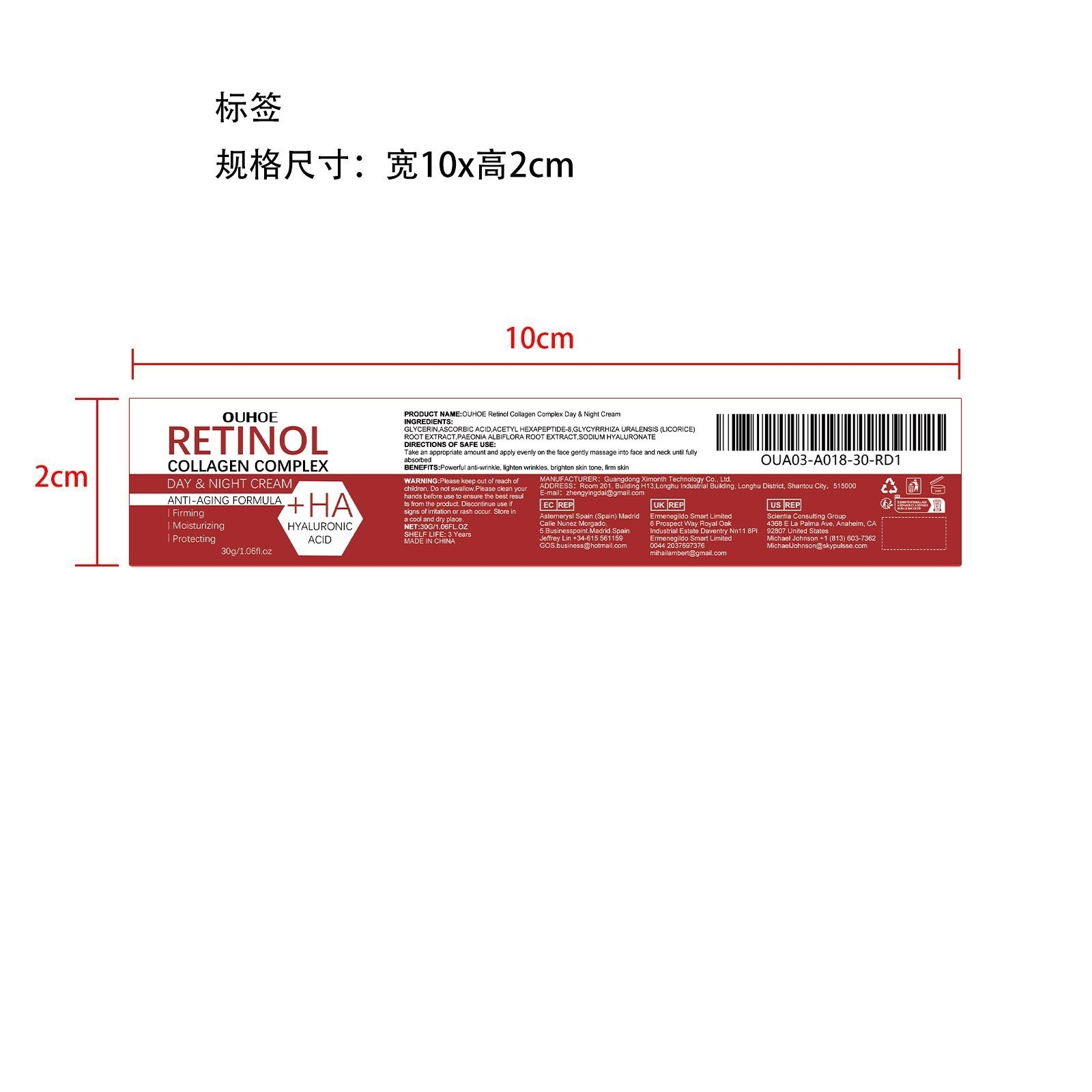 DRUG LABEL: OUHOE Retinol Collagen Complex Day Night Cream
NDC: 84660-027 | Form: CREAM
Manufacturer: Guangdong Ximonth Technology Co., Ltd.
Category: otc | Type: HUMAN OTC DRUG LABEL
Date: 20240926

ACTIVE INGREDIENTS: ASCORBIC ACID 6 g/30 g; ACETYL HEXAPEPTIDE-8 AMIDE 4.5 g/30 g; GLYCYRRHIZA URALENSIS ROOT 4.5 g/30 g; PAEONIA LACTIFLORA ROOT 3 g/30 g
INACTIVE INGREDIENTS: GLYCERIN 9 g/30 g; HYALURONATE SODIUM 3 g/30 g

Active Ingredient(s)

ASCORBIC ACID、ACETYL HEXAPEPTIDE-8、GLYCYRRHIZA URALENSIS (LICORICE) ROOT EXTRACT、PAEONIA ALBIFLORA ROOT EXTRACT

Purpose

Powerful anti-wrinkle, lighten wrinkles, brighten skin tone, firm skin

Use

Take an appropriate amount and apply evenly on the face gently massage into face and neck until fully absorbed

Warnings

Please keep out of reach of children.Do not swallow.Please clean your hands before use to ensure the best results from the product.Discontinue use if signs of irritation or rash occur.Store in a cool and dry place

Do not use

Discontinue use if signs of irritation or rash occur

STOP USE

Discontinue use if signs of irritation or rash occur.

KEEP OUT OF REACH OF CHILDREN

Please keep out of reach of children. Do not swallow

STORAGE AND HANDLING

Avoid freezing and excessive heat above 40C (104F) ）
Store in a cool and dry place.

INACTIVE INGREDIENT

GLYCERIN、SODIUM HYALURONATE